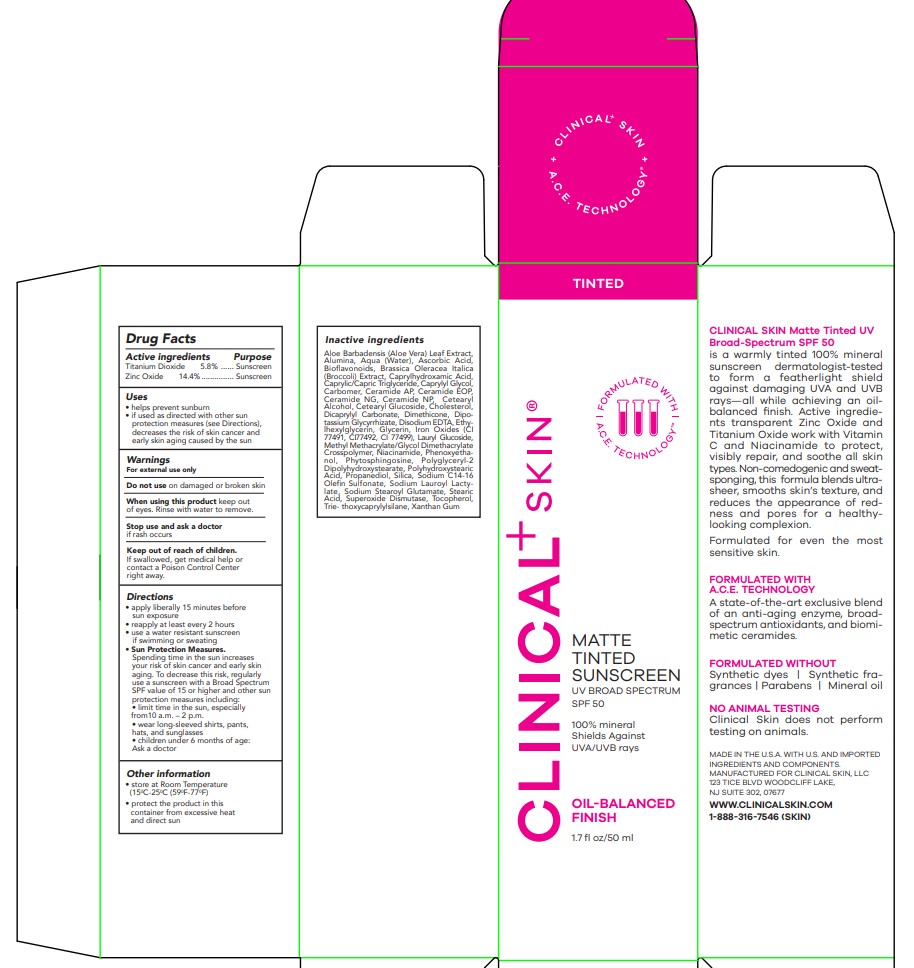 DRUG LABEL: Matte Tinted Sunscreen SPF 50
NDC: 84248-026 | Form: LOTION
Manufacturer: CLINICAL SKIN LLC
Category: otc | Type: HUMAN OTC DRUG LABEL
Date: 20240611

ACTIVE INGREDIENTS: TITANIUM DIOXIDE 5.8 mg/1 mL; ZINC OXIDE 14.4 mg/1 mL
INACTIVE INGREDIENTS: CERAMIDE NG; PROPANEDIOL; ALUMINUM OXIDE; CHOLESTEROL; SODIUM LAUROYL LACTYLATE; ALOE VERA LEAF; WATER; CITRUS BIOFLAVONOIDS; MUSKMELON; CETOSTEARYL ALCOHOL; DISODIUM EDTA-COPPER; POLYGLYCERYL-2 DIPOLYHYDROXYSTEARATE; POLYHYDROXYSTEARIC ACID (2300 MW); TRIETHOXYCAPRYLYLSILANE; BROCCOLI SEED OIL; CERAMIDE AP; MEDIUM-CHAIN TRIGLYCERIDES; GLYCYRRHIZINATE DIPOTASSIUM; FERRIC OXIDE RED; PHYTOSPHINGOSINE; SILICON DIOXIDE; SODIUM C14-16 OLEFIN SULFONATE; CARBOMER HOMOPOLYMER, UNSPECIFIED TYPE; PHENOXYETHANOL; CAPRYLHYDROXAMIC ACID; CERAMIDE NP; DICAPRYLYL CARBONATE; ETHYLHEXYLGLYCERIN; CETEARYL GLUCOSIDE; NIACINAMIDE; STEARIC ACID; XANTHAN GUM; LAURYL GLUCOSIDE; SODIUM STEAROYL GLUTAMATE; CAPRYLYL GLYCOL; TOCOPHEROL; DIMETHICONE; ASCORBIC ACID; GLYCERIN; METHYL METHACRYLATE/GLYCOL DIMETHACRYLATE CROSSPOLYMER

Clinical Skin Matte Tinted Sunscreen

Active Ingredients

Titanium Dioxide 5.8%

Zinc Oxide 14.4%

Purpose

Sunscreen

Use

• helps prevent sunburn

• if used as directed with other sun protection measures (see Directions), decreases the risk of skin cancer and early skin aging caused by the sun

Warnings

For external use only

Do not use

on damaged or broken skin

When using this product

keep out of eyes. Rinse with water to remove.

Stop use and ask a doctor

if rash occurs.

Keep out of reach of children

If swallowed, get medical help or contact a Poison Control Center right away.

Directions

• apply liberally 15 minutes before sun exposure

• reapply at least every 2 hours • use a water resistant sunscreen if swimming or sweating

• Sun Protection Measures. Spending time in the sun increases your risk of skin cancer and early skin aging. To decrease this risk, regularly use a sunscreen with a Broad Spectrum SPF value of 15 or higher and other sun protection measures including:

• limit time in the sun, especially from10 a.m. – 2 p.m.

• wear long-sleeved shirts, pants, hats, and sunglasses

• children under 6 months of age: Ask a doctor

Other Information

• store at Room Temperature (15 C-25 C (59 F-77 F)

• protect the product in this container from excessive heat and direct sun

Inactive ingredients

Aloe Barbadensis (Aloe Vera) Leaf Extract, Alumina, Aqua (Water), Ascorbic Acid, Bioflavonoids, Brassica Oleracea Italica (Broccoli) Extract, Caprylhydroxamic Acid, Caprylic/Capric Triglyceride, Caprylyl Glycol, Carbomer, Ceramide AP, Ceramide EOP, Ceramide NG, Ceramide NP, Cetearyl Alcohol, Cetearyl Glucoside, Cholesterol, Dicaprylyl Carbonate, Dimethicone, Dipotassium Glycyrrhizate, Disodium EDTA, Ethylhexylglycerin, Glycerin, Iron Oxides (CI 77491, CI77492, CI 77499), Lauryl Glucoside, Methyl Methacrylate/Glycol Dimethacrylate Crosspolymer, Niacinamide, Phenoxyethanol, Phytosphingosine, Polyglyceryl-2 Dipolyhydroxystearate, Polyhydroxystearic Acid, Propanediol, Silica, Sodium C14-16 Olefin Sulfonate, Sodium Lauroyl Lactylate, Sodium Stearoyl Glutamate, Stearic Acid, Superoxide Dismutase, Tocopherol, Trie- thoxycaprylylsilane, Xanthan Gum

PACKAGE LABEL

CLINICAL+ SKIN

MATE TINTED SUNSCREEN

UV BROAD SPECTRUM

SPF50

100% MINERAL

SHIELDS AGAINST

UVA/UVB RAYS

OIL-BALANCED

FINISH

1.7 FL OZ/50 ML